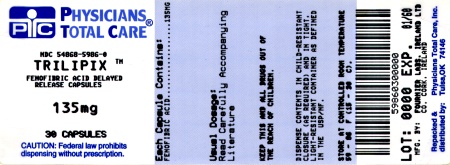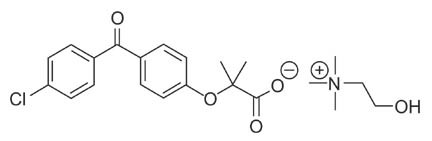 DRUG LABEL: Trilipix
NDC: 54868-5986 | Form: CAPSULE, DELAYED RELEASE
Manufacturer: Physicians Total Care, Inc.
Category: prescription | Type: HUMAN PRESCRIPTION DRUG LABEL
Date: 20111214

ACTIVE INGREDIENTS: FENOFIBRIC ACID 135  mg/1 1
INACTIVE INGREDIENTS: POVIDONE; WATER; HYDROXYPROPYL CELLULOSE; SILICON DIOXIDE; SODIUM STEARYL FUMARATE; TALC; TRIETHYL CITRATE; GELATIN; TITANIUM DIOXIDE; FD&C BLUE NO. 2; FERRIC OXIDE YELLOW; HYPROMELLOSES

HIGHLIGHTS OF PRESCRIBING INFORMATION

These highlights do not include all the information needed to use Trilipix safely and effectively. See full prescribing information for Trilipix.
Trilipix (fenofibric acid) capsule, delayed release for oral use
Initial U.S. Approval: 2008

1 INDICATIONS AND USAGE

Trilipix is a peroxisome proliferator receptor alpha (PPARα) activator indicated:

- In combination with a statin to reduce TG and increase HDL-C in patients with mixed dyslipidemia and CHD or a CHD risk equivalent who are on optimal statin therapy to achieve their LDL-C goal (1.1).
- As monotherapy to reduce TG in patients with severe hypertriglyceridemia (1.2).
- As monotherapy to reduce elevated LDL-C, Total-C, TG and Apo B, and to increase HDL-C in patients with primary hyperlipidemia or mixed dyslipidemia (1.3).

Important Limitations of Use: No incremental benefit of Trilipix on cardiovascular morbidity and mortality over and above that demonstrated for statin monotherapy has been established. Fenofibrate at a dose equivalent to 135 mg of Trilipix was not shown to reduce coronary heart disease morbidity and mortality in 2 large, randomized controlled trials of patients with type 2 diabetes mellitus.

2 DOSAGE AND ADMINISTRATION

- Mixed dyslipidemia: 135 mg once daily (2.2).
- Hypertriglyceridemia: 45 to 135 mg once daily (2.3).
- Renally impaired patients: 45 mg once daily (2.5).
- Maximum dose: 135 mg once daily (2.1).
- May be taken without regard to food (2.1).
- May be taken at the same time as a statin (2.2).
- Co-administration with the maximum dose of a statin has not been evaluated in clinical studies and should be avoided unless the benefits are expected to outweigh the risks (2.2).

3 DOSAGE FORMS AND STRENGTHS

Oral Delayed Release Capsules: 45 mg and 135 mg (3).

4 CONTRAINDICATIONS

- Severe renal dysfunction, including patients receiving dialysis (4, 12.3).
- Active liver disease (4, 5.3).
- Gallbladder disease (4, 5.4).
- Nursing mothers (4, 8.3).

5 WARNINGS AND PRECAUTIONS

- Myopathy and rhabdomyolysis have been reported in patients taking fenofibrate. The risks for myopathy and rhabdomyolysis are increased when fibrates are co-administered with a statin (with a significantly higher rate observed for gemfibrozil), particularly in elderly patients and patients with diabetes, renal failure, or hypothyroidism (5.1).
- Trilipix can increase serum transaminases. Liver tests should be monitored periodically (5.3).
- Trilipix can reversibly increase serum creatinine levels (5.2). Renal function should be monitored periodically in patients with renal insufficiency (8.6).
- Trilipix increases cholesterol excretion into the bile, leading to risk of cholelithiasis. If cholelithiasis is suspected, gallbladder studies are indicated (5.4).
- Exercise caution in concomitant treatment with oral coumarin anticoagulants. Adjust the dosage of coumarin anticoagulant to maintain the prothrombin time/INR at the desired level to prevent bleeding complications (5.5).

6 ADVERSE REACTIONS

The most common adverse events (≥ 3% of patients receiving Trilipix or Trilipix co-administered with statins) are headache, back pain, nasopharyngitis, nausea, myalgia, diarrhea, and upper respiratory tract infection (6.1).

To report SUSPECTED ADVERSE REACTIONS, contact Abbott Laboratories at 1-800-633-9110 or FDA at 1-800-FDA-1088 or www.fda.gov/medwatch

7 DRUG INTERACTIONS

- Coumarin Anticoagulants: (7.1).
- Bile Acid Resins: (7.2).
- Cyclosporine: (7.3).

8 USE IN SPECIFIC POPULATIONS

- Geriatric Use: Dose selection for the elderly should be made on the basis of renal function (8.5).
- Renal Impairment: Trilipix should be avoided in patients with severe renal impairment. Dose adjustment is required in patients with mild to moderate renal impairment (8.6).
- The use of Trilipix has not been evaluated in patients with hepatic impairment (8.7).

FULL PRESCRIBING INFORMATION

1 INDICATIONS AND USAGE

1.1 Co-administration Therapy with Statins for the Treatment of Mixed Dyslipidemia

Trilipix is indicated as an adjunct to diet in combination with a statin to reduce TG and increase HDL-C in patients with mixed dyslipidemia and CHD or a CHD risk equivalent who are on optimal statin therapy to achieve their LDL-C goal.

CHD risk equivalents comprise:

- Other clinical forms of atherosclerotic disease (peripheral arterial disease, abdominal aortic aneurysm, and symptomatic carotid artery disease);
- Diabetes;
- Multiple risk factors that confer a 10-year risk for CHD > 20%

1.2 Treatment of Severe Hypertriglyceridemia

Trilipix is indicated as adjunctive therapy to diet to reduce TG in patients with severe hypertriglyceridemia. Improving glycemic control in diabetic patients showing fasting chylomicronemia will usually obviate the need for pharmacological intervention. Markedly elevated levels of serum triglycerides (e.g. > 2,000 mg/dL) may increase the risk of developing pancreatitis. The effect of Trilipix therapy on reducing this risk has not been adequately studied.

1.3 Treatment of Primary Hyperlipidemia or Mixed Dyslipidemia

Trilipix is indicated as adjunctive therapy to diet to reduce elevated LDL-C, Total-C, TG, and Apo B, and to increase HDL-C in patients with primary hyperlipidemia or mixed dyslipidemia.

1.4 Important Limitations of Use

No incremental benefit of Trilipix on cardiovascular morbidity and mortality over and above that demonstrated for statin monotherapy has been established. Fenofibrate at a dose equivalent to 135 mg of Trilipix was not shown to reduce coronary heart disease morbidity and mortality in 2 large, randomized controlled trials of patients with type 2 diabetes mellitus.

1.5 General Considerations for Treatment

Laboratory studies should be performed to establish that lipid levels are abnormal before instituting Trilipix therapy.

Every reasonable attempt should be made to control serum lipids with non-drug methods including appropriate diet, exercise, weight loss in obese patients, and control of any medical problems such as diabetes mellitus and hypothyroidism that may be contributing to the lipid abnormalities. Medications known to exacerbate hypertriglyceridemia (beta-blockers, thiazides, estrogens) should be discontinued or changed if possible, and excessive alcohol intake should be addressed before triglyceride-lowering drug therapy is considered. If the decision is made to use lipid-altering drugs, the patient should be instructed that this does not reduce the importance of adhering to diet.

Drug therapy is not indicated for patients who have elevations of chylomicrons and plasma triglycerides, but who have normal levels of VLDL.

2 DOSAGE AND ADMINISTRATION

2.1 General Considerations

Patients should be placed on an appropriate lipid-lowering diet before receiving Trilipix as monotherapy or co-administered with a statin [see DOSAGE AND ADMINISTRATION (2.2, 2.3 and 2.4)], and should continue this diet during treatment. Trilipix delayed release capsules can be taken without regard to meals. Serum lipids should be monitored periodically. The maximum dose is 135 mg once daily.

2.2 Co-administration Therapy with Statins for the Treatment of Mixed Dyslipidemia

Trilipix 135 mg may be co-administered with an HMG-CoA reductase inhibitor (statin) in patients with mixed dyslipidemia. For convenience, the daily dose of Trilipix may be taken at the same time as a statin, according to the dosing recommendations for each medication. Co-administration with the maximum dose of a statin has not been evaluated in clinical studies and should be avoided unless the benefits are expected to outweigh the risks.

2.3 Severe Hypertriglyceridemia

The initial dose of Trilipix is 45 to 135 mg once daily. Dosage should be individualized according to patient response, and should be adjusted if necessary following repeat lipid determinations at 4 to 8 week intervals. The maximum dose is 135 mg once daily.

2.4 Primary Hyperlipidemia or Mixed Dyslipidemia

The dose of Trilipix is 135 mg once daily.

2.5 Impaired Renal Function

Treatment with Trilipix should be initiated at a dose of 45 mg once daily in patients with mild to moderate renal impairment and should only be increased after evaluation of the effects on renal function and lipid levels at this dose. The use of Trilipix should be avoided in patients with severely impaired renal function.

2.6 Elderly Patients

Dose selection for the elderly should be made on the basis of renal function [see USE IN SPECIFIC POPULATIONS (8.5)].

3 DOSAGE FORMS AND STRENGTHS

- 45 mg choline fenofibrate delayed release capsules with a reddish-brown cap imprinted in white ink the Abbott “A” logo and a yellow body imprinted in black ink the number “45”.
- 135 mg choline fenofibrate delayed release capsules with a blue cap imprinted in white ink the Abbott “A” logo and a yellow body imprinted in black ink the number “135”.

4 CONTRAINDICATIONS

Trilipix is contraindicated in:

- patients with severe renal impairment, including those receiving dialysis.
- patients with active liver disease, including those with primary biliary cirrhosis and unexplained persistent liver function abnormalities.
- patients with preexisting gallbladder disease.
- nursing mothers.
- patients with hypersensitivity to fenofibric acid, choline fenofibrate or fenofibrate [see WARNINGS and PRECAUTIONS (5.7)].

When Trilipix is co-administered with a statin, refer to the Contraindications section of the respective statin labeling.

5 WARNINGS AND PRECAUTIONS

5.1 Skeletal Muscle

Fibrate and statin monotherapy increase the risk of myositis or myopathy, and have been associated with rhabdomyolysis. Data from observational studies suggest that the risk for rhabdomyolysis is increased when fibrates are co-administered with a statin (with a significantly higher rate observed for gemfibrozil). Refer to the respective statin labeling for important drug-drug interactions that increase statin levels and could increase this risk. The risk for serious muscle toxicity appears to be increased in elderly patients and in patients with diabetes, renal failure, or hypothyroidism.

Myalgia was reported in 3.3% of patients treated with Trilipix monotherapy and 3.1% to 3.5% of patients treated with Trilipix co-administered with statins compared to 4.7% to 6.1% of patients treated with statin monotherapy. Increases in creatine phosphokinase (CPK) to > 5 times upper limit of normal occurred in no patients treated with Trilipix monotherapy and 0.2% to 1.2% of patients treated with Trilipix co-administered with statins compared to 0.4% to 1.3% of patients treated with statin monotherapy.

Myopathy should be considered in any patient with diffuse myalgias, muscle tenderness or weakness, and/or marked elevations of CPK levels. Patients should promptly report unexplained muscle pain, tenderness or weakness, particularly if accompanied by malaise or fever. CPK levels should be assessed in patients reporting these symptoms, and Trilipix and statin therapy should be discontinued if markedly elevated CPK levels occur or myopathy or myositis is diagnosed.

5.2 Serum Creatinine

Reversible elevations in serum creatinine have been reported in patients receiving Trilipix as monotherapy or co-administered with statins as well as patients receiving fenofibrate. In the pooled analysis of three double-blind controlled studies of Trilipix administered as monotherapy or in combination with statins, increases in creatinine to > 2 mg/dL occurred in 0.8% of patients treated with Trilipix monotherapy and 1.1% to 1.3% of patients treated with Trilipix co-administered with statins compared to 0% to 0.4% of patients treated with statin monotherapy. Elevations in serum creatinine were generally stable over time with no evidence for continued increases in serum creatinine with long-term therapy and tended to return to baseline following discontinuation of treatment. The clinical significance of these observations is unknown. Monitoring renal function in patients with renal impairment taking Trilipix is suggested. Renal monitoring should be considered for patients at risk for renal insufficiency, such as the elderly and those with diabetes.

5.3 Liver Function

Trilipix at a dose of 135 mg once daily administered as monotherapy or co-administered with low to moderate doses of statins has been associated with increases in serum transaminases [AST (SGOT) or ALT (SGPT)]. In a pooled analysis of three double-blind controlled studies of Trilipix administered as monotherapy or in combination with statins, increases to > 3 times the upper limit of normal on two consecutive occasions in ALT and AST occurred in 1.9% and 0.2%, respectively, of patients receiving Trilipix monotherapy and in 1.3% and 0.4%, respectively, of patients receiving Trilipix co-administered with statins. Increases to > 3 times the upper limit of normal in ALT and AST occurred in no patients receiving low- to moderate-dose statin monotherapy. Increases to > 3 times the upper limit of normal in ALT and AST occurred in 0.8% and 0.4%, respectively in patients receiving high-dose statin monotherapy. In a long-term study of Trilipix co-administered with statins for up to 52 weeks, increases of > 3 times the upper limit of normal on two consecutive occasions of ALT and AST occurred in 1.2% and 0.5% of patients, respectively. When transaminase determinations were followed either after discontinuation of treatment or during continued treatment, a return to normal limits was usually observed. Increases in ALT and/or AST were not accompanied by increases in bilirubin or clinically significant increases in alkaline phosphatase.

In a pooled analysis of 10 placebo-controlled trials of fenofibrate, increases to > 3 times the upper limit of normal in ALT occurred in 5.3% of patients taking fenofibrate versus 1.1% of patients treated with placebo. The incidence of increases in transaminases observed with fenofibrate therapy may be dose related. In an 8-week dose-ranging study of fenofibrate in hypertriglyceridemia, the incidence of ALT or AST elevations ≥ 3 times the upper limit of normal was 13% in patients receiving dosages equivalent to 90 mg to 135 mg Trilipix once daily and was 0% in those receiving dosages equivalent to 45 mg Trilipix once daily or less, or placebo. Hepatocellular, chronic active, and cholestatic hepatitis observed with fenofibrate therapy have been reported after exposures of weeks to several years. In extremely rare cases, cirrhosis has been reported in association with chronic active hepatitis.

Regular monitoring of liver function, including serum ALT (SGPT) should be performed for the duration of therapy with Trilipix, and therapy discontinued if enzyme levels persist above 3 times the upper limit of normal.

5.4 Cholelithiasis

Trilipix, like fenofibrate, clofibrate, and gemfibrozil, may increase cholesterol excretion into the bile, potentially leading to cholelithiasis. If cholelithiasis is suspected, gallbladder studies are indicated. Trilipix therapy should be discontinued if gallstones are found.

5.5 Concomitant Oral Anticoagulants

Caution should be exercised when Trilipix is given in conjunction with oral coumarin anticoagulants. Trilipix may potentiate the anticoagulant effects of these agents resulting in prolongation of the prothrombin time/INR. Frequent monitoring of prothrombin time/INR and dose adjustment of the oral anticoagulant are recommended until the prothrombin time/INR has stabilized in order to prevent bleeding complications.

5.6 Pancreatitis

Pancreatitis has been reported in patients taking drugs of the fibrate class, including Trilipix. This occurrence may represent a failure of efficacy in patients with severe hypertriglyceridemia, a direct drug effect, or a secondary phenomenon mediated through biliary tract stone or sludge formation with obstruction of the common bile duct.

5.7 Hypersensitivity Reactions

Acute hypersensitivity reactions including severe skin rashes requiring patient hospitalization and treatment with steroids have occurred very rarely during treatment with fenofibrate, including rare spontaneous reports of Stevens-Johnson Syndrome and toxic epidermal necrolysis.

5.8 Hematological Changes

Mild to moderate hemoglobin, hematocrit, and white blood cell decreases have been observed in patients following initiation of Trilipix and fenofibrate therapy. Extremely rare spontaneous reports of thrombocytopenia and agranulocytosis have been received with fenofibrate therapy.

5.9 Mortality and Coronary Heart Disease Morbidity

The effect of Trilipix on coronary heart disease morbidity and mortality and non-cardiovascular mortality has not been established. Because of similarities between Trilipix and fenofibrate, clofibrate, and gemfibrozil, the findings in the following large randomized, placebo-controlled clinical studies with these fibrate drugs may also apply to Trilipix.

The Action to Control Cardiovascular Risk in Diabetes Lipid (ACCORD Lipid) trial was a randomized placebo-controlled study of 5518 patients with type 2 diabetes mellitus on background statin therapy treated with fenofibrate. The mean duration of follow-up was 4.7 years. Fenofibrate plus statin combination therapy showed a non-significant 8% relative risk reduction in the primary outcome of major adverse cardiovascular events (MACE), a composite of non-fatal myocardial infarction, non-fatal stroke, and cardiovascular disease death (hazard ratio [HR] 0.92, 95% CI 0.79-1.08) (p=0.32) as compared to statin monotherapy. In a gender subgroup analysis, the hazard ratio for MACE in men receiving combination therapy versus statin monotherapy was 0.82 (95% CI 0.69-0.99), and the hazard ratio for MACE in women receiving combination therapy versus statin monotherapy was 1.38 (95% CI 0.98-1.94) (interaction p=0.01). The clinical significance of this subgroup finding is unclear.

The Fenofibrate Intervention and Event Lowering in Diabetes (FIELD) study was a 5-year randomized, placebo-controlled study of 9795 patients with type 2 diabetes mellitus treated with fenofibrate. Fenofibrate demonstrated a non-significant 11% relative reduction in the primary outcome of coronary heart disease events (hazard ratio [HR] 0.89, 95% CI 0.75-1.05, p = 0.16) and a significant 11% reduction in the secondary outcome of total cardiovascular disease events (HR 0.89 [0.80-0.99], p = 0.04). There was a non-significant 11% (HR 1.11 [0.95, 1.29], p = 0.18) and 19% (HR 1.19 [0.90, 1.57], p = 0.22) increase in total and coronary heart disease mortality, respectively, with fenofibrate as compared to placebo.

In the Coronary Drug Project, a large study of post-myocardial infarction patients treated for 5 years with clofibrate, there was no difference in mortality seen between the clofibrate group and the placebo group. There was, however, a difference in the rate of cholelithiasis and cholecystitis requiring surgery between the two groups (3.0% vs. 1.8%).

In a study conducted by the World Health Organization (WHO), 5000 subjects without known coronary artery disease were treated with placebo or clofibrate for 5 years and followed for an additional one year. There was a statistically significant, higher age-adjusted all-cause mortality in the clofibrate group compared with the placebo group (5.70% vs. 3.96%, p = < 0.01). Excess mortality was due to a 33% increase in non-cardiovascular causes, including malignancy, post-cholecystectomy complications, and pancreatitis. This appeared to confirm the higher risk of gallbladder disease seen in clofibrate-treated patients studied in the Coronary Drug Project.

The Helsinki Heart Study was a large (N = 4081) study of middle-aged men without a history of coronary artery disease. Subjects received either placebo or gemfibrozil for 5 years, with a 3.5 year open extension afterward. Total mortality was numerically higher in the gemfibrozil randomization group but did not achieve statistical significance (p = 0.19, 95% confidence interval for relative risk G:P = 0.91-1.64). Although cancer deaths trended higher in the gemfibrozil group (p = 0.11), cancers (excluding basal cell carcinoma) were diagnosed with equal frequency in both study groups. Due to the limited size of the study, the relative risk of death from any cause was not shown to be different than that seen in the 9 year follow-up data from WHO study (RR = 1.29). A secondary prevention component of the Helsinki Heart Study enrolled middle-aged men excluded from the primary prevention study because of known or suspected coronary heart disease. Subjects received gemfibrozil or placebo for 5 years. Although cardiac deaths trended higher in the gemfibrozil group, this was not statistically significant (hazard ratio 2.2, 95% confidence interval: 0.94-5.05).

5.10 Venothromboembolic Disease

In the FIELD trial, pulmonary embolus (PE) and deep vein thrombosis (DVT) were observed at higher rates in the fenofibrate- than the placebo-treated group. Of 9,795 patients enrolled in FIELD, there were 4,900 in the placebo group and 4,895 in the fenofibrate group. For DVT, there were 48 events (1%) in the placebo group and 67 (1%) in the fenofibrate group (p = 0.074); and for PE, there were 32 (0.7%) events in the placebo group and 53 (1%) in the fenofibrate group (p = 0.022).

In the Coronary Drug Project, a higher proportion of the clofibrate group experienced definite or suspected fatal or nonfatal PE or thrombophlebitis than the placebo group (5.2% vs. 3.3% at five years; p < 0.01).

6 ADVERSE REACTIONS

6.1 Clinical Studies Experience

Because clinical studies are conducted under widely varying conditions, adverse event rates observed in the clinical studies of a drug cannot be directly compared to rates in the clinical studies of another drug.

Trilipix (fenofibric acid)

Monotherapy

Treatment-emergent adverse events reported in 3% or more of patients treated with Trilipix during the randomized controlled trials are listed in Table 1 below.

Co-Administration Therapy with Statins (Double-blind Controlled Trials)

Treatment-emergent adverse events reported in 3% or more of patients treated with Trilipix co-administered with statins during the randomized controlled trials are listed in Table 1 below.

Table 1.Treatment-Emergent Adverse Events Reported in ≥ 3% of Patients Receiving Trilipix or Trilipix Co-Administered with a Statin During Double-Blind Controlled Studies [Number (%)]
Adverse Event | Trilipix (N = 490) | Low-Dose Statin (N = 493) | Trilipix + Low-Dose Statin (N = 490) | Moderate-Dose Statin (N = 491) | Trilipix + Moderate-Dose Statin (N = 489) | High-Dose Statin (N = 245)
Gastrointestinal Disorders
Constipation | 16 (3.3) | 11 (2.2) | 16 (3.3) | 13 (2.6) | 15 (3.1) | 6 (2.4)
Diarrhea | 19 (3.9) | 16 (3.2) | 15 (3.1) | 24 (4.9) | 18 (3.7) | 17 (6.9)
Dyspepsia | 18 (3.7) | 13 (2.6) | 13 (2.7) | 17 (3.5) | 23 (4.7) | 6 (2.4)
Nausea | 21 (4.3) | 18 (3.7) | 17 (3.5) | 22 (4.5) | 27 (5.5) | 10 (4.1)
General Disorders and Administration Site Conditions
Fatigue | 10 (2.0) | 13 (2.6) | 13 (2.7) | 13 (2.6) | 16 (3.3) | 5 (2.0)
Pain | 17 (3.5) | 9 (1.8) | 16 (3.3) | 8 (1.6) | 7 (1.4) | 8 (3.3)
Infections and Infestations
Nasopharyngitis | 17 (3.5) | 29 (5.9) | 23 (4.7) | 16 (3.3) | 21 (4.3) | 9 (3.7)
Sinusitis | 16 (3.3) | 4 (0.8) | 14 (2.9) | 8 (1.6) | 17 (3.5) | 4 (1.6)
Upper Respiratory Tract Infection | 26 (5.3) | 13 (2.6) | 18 (3.7) | 23 (4.7) | 23 (4.7) | 7 (2.9)
Investigations
ALT Increased | 6 (1.2) | 2 (0.4) | 15 (3.1) | 2 (0.4) | 12 (2.5) | 4 (1.6)
Musculoskeletal and Connective Tissue Disorders
Arthralgia | 19 (3.9) | 22 (4.5) | 21 (4.3) | 21 (4.3) | 17 (3.5) | 12 (4.9)
Back Pain | 31 (6.3) | 31 (6.3) | 30 (6.1) | 32 (6.5) | 20 (4.1) | 8 (3.3)
Muscle Spasms | 8 (1.6) | 18 (3.7) | 12 (2.4) | 24 (4.9) | 15 (3.1) | 6 (2.4)
Myalgia | 16 (3.3) | 24 (4.9) | 17 (3.5) | 23 (4.7) | 15 (3.1) | 15 (6.1)
Pain in Extremity | 22 (4.5) | 24 (4.9) | 14 (2.9) | 21 (4.3) | 13 (2.7) | 9 (3.7)
Nervous System Disorders
Dizziness | 20 (4.1) | 8 (1.6) | 19 (3.9) | 11 (2.2) | 16 (3.3) | 2 (0.8)
Headache | 62 (12.7) | 64 (13.0) | 64 (13.1) | 82 (16.7) | 58 (11.9) | 32 (13.1)
Low-dose statin = rosuvastatin 10 mg, simvastatin 20 mg, or atorvastatin 20 mg
Moderate-dose statin = rosuvastatin 20 mg, simvastatin 40 mg, or atorvastatin 40 mg
High-dose statin = rosuvastatin 40 mg, simvastatin 80 mg, or atorvastatin 80 mg

Co-Administration Therapy with Statins (Long-Term Exposure for up to 64 Weeks)

Patients successfully completing any one of the three double-blind, controlled studies were eligible to participate in a 52-week long-term extension study where they received Trilipix co-administered with the moderate dose statin. A total of 2201 patients received at least one dose of Trilipix co-administered with a statin in the double-blind controlled study or the long-term extension study for up to a total of 64 weeks of treatment. Additional treatment-emergent adverse events (not listed in Table 1 above) reported in 3% or more of patients receiving Trilipix co-administered with a statin in either the double-blind controlled studies or the long-term extension study are provided below.

Infections and Infestations
Bronchitis, influenza, and urinary tract infection.

Investigations
AST increased, blood CPK increased, and hepatic enzyme increased.

Musculoskeletal and Connective Tissue Disorders
Musculoskeletal pain.

Psychiatric Disorders
Insomnia.

Respiratory, Thoracic, and Mediastinal Disorders
Cough and pharyngolaryngeal pain.

Vascular Disorders
Hypertension.

Fenofibrate

Fenofibric acid is the active metabolite of fenofibrate. Adverse events reported by 2% or more of patients treated with fenofibrate and greater than placebo during double-blind, placebo-controlled trials are listed in Table 2. Adverse events led to discontinuation of treatment in 5.0% of patients treated with fenofibrate and in 3.0% treated with placebo. Increases in liver tests were the most frequent events, causing discontinuation of fenofibrate treatment in 1.6% of patients in double-blind trials.

Table 2. Adverse Events Reported by 2% or More of Patients Treated with Fenofibrate and Greater than Placebo During the Double-Blind, Placebo-Controlled Trials
BODY SYSTEM Adverse Event | Fenofibrate* (N = 439) | Placebo (N = 365)
BODY AS A WHOLE
Abdominal Pain | 4.6% | 4.4%
Back Pain | 3.4% | 2.5%
Headache | 3.2% | 2.7%
DIGESTIVE
Nausea | 2.3% | 1.9%
Constipation | 2.1% | 1.4%
INVESTIGATIONS
Abnormal Liver Tests | 7.5% | 1.4%
Increased AST | 3.4% | 0.5%
Increased ALT | 3.0% | 1.6%
Increased Creatine Phosphokinase | 3.0% | 1.4%
RESPIRATORY
Respiratory Disorder | 6.2% | 5.5%
Rhinitis | 2.3% | 1.1%
* Dosage equivalent to 135 mg Trilipix

The following adverse events have been identified during postapproval use of fenofibrate: myalgia, rhabdomyolysis, increased creatine phosphokinase, pancreatitis, increased alanine aminotransaminase, increased aspartate aminotransaminase, renal failure, muscle spasms, acute renal failure, hepatitis, cirrhosis, nausea, abdominal pain, anemia, headache, arthralgia, and asthenia. Because these events are reported voluntarily from a population of uncertain size, it is not always possible to reliably estimate their frequency or establish a casual relationship to drug exposure.

7 DRUG INTERACTIONS

7.1 Oral Anticoagulants

Caution should be exercised when oral coumarin anticoagulants are given in conjunction with Trilipix [see WARNINGS AND PRECAUTIONS (5.5)].

7.2 Bile Acid Resins

Since bile acid resins may bind other drugs given concurrently, patients should take Trilipix at least 1 hour before or 4-6 hours after a bile acid resin to avoid impeding its absorption.

7.3 Cyclosporine

Because cyclosporine can produce nephrotoxicity with decreases in creatinine clearance and rises in serum creatinine, and because renal excretion is the primary elimination route of drugs of the fibrate class including Trilipix, there is a risk that an interaction will lead to decline of renal function. The benefits and risks of using Trilipix with immunosuppressants and other potentially nephrotoxic agents should be carefully considered, and the lowest effective dose employed.

8 USE IN SPECIFIC POPULATIONS

8.1 Pregnancy

Pregnancy Category: C

The safety of Trilipix in pregnant women has not been established. There are no adequate and well controlled studies of Trilipix in pregnant women. Trilipix should be used during pregnancy only if the potential benefit justifies the potential risk to the fetus.

When Trilipix is administered with a statin in a woman of childbearing potential, refer to pregnancy category and product labeling for the statin [see Precautions, Pregnancy]. All statins are contraindicated in pregnant women.

In pregnant rats given oral dietary doses of 14, 127, and 361 mg/kg/day from gestation day 6-15 during the period of organogenesis, adverse developmental findings were not observed at 14 mg/kg/day (less than 1 times the maximum recommended human dose [MRHD], based on body surface area comparisons; mg/m^2). At higher multiples of human doses evidence of maternal toxicity was observed.

In pregnant rabbits given oral gavage doses of 15, 150, and 300 mg/kg/day from gestation day 6-18 during the period of organogenesis and allowed to deliver, aborted litters were observed at 150 mg/kg/day (10 times the MRHD, based on body surface area comparisons; mg/m^2). No developmental findings were observed at 15 mg/kg/day (at less than 1 times the MRHD, based on body surface area comparisons; mg/m^2).

In pregnant rats given oral dietary doses of 15, 75, and 300 mg/kg/day from gestation day 15 through lactation day 21 (weaning), maternal toxicity was observed at less than 1 times the MRHD, based on body surface area comparisons; mg/m^2.

8.3 Nursing Mothers

Trilipix should not be used in nursing mothers. A decision should be made whether to discontinue nursing or to discontinue the drug.

8.4 Pediatric Use

The safety and effectiveness of Trilipix monotherapy or co-administration with a statin in pediatric patients have not been established.

8.5 Geriatric Use

Trilipix is substantially excreted by the kidney as fenofibric acid and fenofibric acid glucuronide, and the risk of adverse reactions to this drug may be greater in patients with impaired renal function. Since elderly patients have a higher incidence of renal impairment, the dose selection for the elderly should be made on the basis of renal function [see CLINICAL PHARMACOLOGY (12.3)]. Consider monitoring renal function in elderly patients taking Trilipix.

8.6 Renal Impairment

The use of Trilipix should be avoided in patients who have severe renal impairment. Dose reduction is required in patients with mild to moderate renal impairment [see CLINICAL PHARMACOLOGY (12.3) and DOSAGE AND ADMINISTRATION (2.5)]. Monitoring renal function in patients with renal impairment is recommended.

8.7 Hepatic Impairment

The use of Trilipix has not been evaluated in subjects with hepatic impairment [see CONTRAINDICATIONS (4) and CLINICAL PHARMACOLOGY (12.3)].

10 OVERDOSAGE

There is no specific treatment for overdose with Trilipix. General supportive care of the patient is indicated, including monitoring of vital signs and observation of clinical status, should an overdose occur. If indicated, elimination of unabsorbed drug should be achieved by emesis or gastric lavage; usual precautions should be observed to maintain the airway. Because Trilipix is highly bound to plasma proteins, hemodialysis should not be considered.

11 DESCRIPTION

Trilipix (fenofibric acid) is a lipid regulating agent available as delayed release capsules for oral administration. Each delayed release capsule contains choline fenofibrate, equivalent to 45 mg or 135 mg of fenofibric acid. The chemical name for choline fenofibrate is ethanaminium, 2-hydroxy-N,N,N-trimethyl, 2-{4-(4-chlorobenzoyl)phenoxy] -2-methylpropanoate (1:1) with the following structural formula:

The empirical formula is C22H28ClNO5 and the molecular weight is 421.91. Choline fenofibrate is freely soluble in water. The melting point is approximately 210°C. Choline fenofibrate is a white to yellow powder, which is stable under ordinary conditions.

Each delayed release capsule contains enteric coated mini-tablets comprised of choline fenofibrate and the following inactive ingredients: hypromellose, povidone, water, hydroxylpropyl cellulose, colloidal silicon dioxide, sodium stearyl fumarate, methacrylic acid copolymer, talc, triethyl citrate. The capsule shell of the 45 mg capsule contains the following inactive ingredients: gelatin, titanium dioxide, yellow iron oxide, black iron oxide, and red iron oxide. The capsule shell of the 135 mg capsule contains the following inactive ingredients: gelatin, titanium dioxide, yellow iron oxide, and FD&C Blue #2.

12 CLINICAL PHARMACOLOGY

12.1 Mechanism of Action

The active moiety of Trilipix is fenofibric acid. The pharmacological effects of fenofibric acid in both animals and humans have been extensively studied through oral administration of fenofibrate.

The lipid-modifying effects of fenofibric acid seen in clinical practice have been explained in vivo in transgenic mice and in vitro in human hepatocyte cultures by the activation of peroxisome proliferator activated receptor α (PPARα). Through this mechanism, fenofibric acid increases lipolysis and elimination of triglyceride-rich particles from plasma by activating lipoprotein lipase and reducing production of Apo CIII (an inhibitor of lipoprotein lipase activity).

The resulting decrease in TG produces an alteration in the size and composition of LDL from small, dense particles (which are thought to be atherogenic due to their susceptibility to oxidation), to large buoyant particles. These larger particles have a greater affinity for cholesterol receptors and are catabolized rapidly. Activation of PPARα also induces an increase in the synthesis of HDL-C and Apo AI and AII.

12.2 Pharmacodynamics

Elevated levels of Total-C, LDL-C, and Apo B, and decreased levels of HDL-C and its transport complex, Apo AI and Apo AII, are risk factors for human atherosclerosis. Epidemiologic studies have established that cardiovascular morbidity and mortality vary directly with the levels of Total-C, LDL-C, and TG, and inversely with the level of HDL-C. The independent effect of raising HDL-C or lowering TG on the risk of cardiovascular morbidity and mortality has not been determined.

12.3 Pharmacokinetics

Trilipix contains fenofibric acid, which is the only circulating pharmacologically active moiety in plasma after oral administration of Trilipix. Fenofibric acid is also the circulating pharmacologically active moiety in plasma after oral administration of fenofibrate, the ester of fenofibric acid.

Plasma concentrations of fenofibric acid after administration of one 135 mg Trilipix delayed release capsule are equivalent to those after one 200 mg capsule of micronized fenofibrate administered under fed conditions.

Absorption
Fenofibric acid is well absorbed throughout the gastrointestinal tract. The absolute bioavailability of fenofibric acid is approximately 81%.

Peak plasma levels of fenofibric acid occur within 4 to 5 hours after a single dose administration of Trilipix capsule under fasting conditions.

Fenofibric acid exposure in plasma, as measured by Cmax and AUC, is not significantly different when a single 135 mg dose of Trilipix is administered under fasting or nonfasting conditions.

Distribution
Upon multiple dosing of Trilipix, fenofibric acid levels reach steady state within 8 days. Plasma concentrations of fenofibric acid at steady state are approximately slightly more than double those following a single dose. Serum protein binding is approximately 99% in normal and dyslipidemic subjects.

Metabolism
Fenofibric acid is primarily conjugated with glucuronic acid and then excreted in urine. A small amount of fenofibric acid is reduced at the carbonyl moiety to a benzhydrol metabolite which is, in turn, conjugated with glucuronic acid and excreted in urine.

In vivo metabolism data after fenofibrate administration indicate that fenofibric acid does not undergo oxidative metabolism (e.g., cytochrome P450) to a significant extent.

Excretion
After absorption, Trilipix is primarily excreted in the urine in the form of fenofibric acid and fenofibric acid glucuronide.

Fenofibric acid is eliminated with a half-life of approximately 20 hours, allowing once daily administration of Trilipix.

Specific Populations
Geriatrics
In five elderly volunteers 77 to 87 years of age, the oral clearance of fenofibric acid following a single oral dose of fenofibrate was 1.2 L/h, which compares to 1.1 L/h in young adults. This indicates that an equivalent dose of Trilipix can be used in elderly subjects with normal renal function, without increasing accumulation of the drug or metabolites [see USE IN SPECIFIC POPULATIONS (8.5)].

Pediatrics
Trilipix has not been investigated in adequate and well-controlled trials in pediatric patients.

Gender
No pharmacokinetic difference between males and females has been observed for Trilipix.

Race
The influence of race on the pharmacokinetics of Trilipix has not been studied.

Renal Impairment
The pharmacokinetics of fenofibric acid was examined in patients with mild, moderate, and severe renal impairment. Patients with severe renal impairment (creatinine clearance [CrCl] < 30 mL/min showed a 2.7-fold increase in exposure for fenofibric acid and increased accumulation of fenofibric acid during chronic dosing compared to that of healthy subjects. Patients with mild to moderate renal impairment (CrCl 30-80 mL/min) had similar exposure but an increase in the half-life for fenofibric acid compared to that of healthy subjects. Based on these findings, the use of Trilipix should be avoided in patients who have severe renal impairment and dose reduction is required in patients having mild to moderate renal impairment.

Hepatic Impairment
No pharmacokinetic studies have been conducted in patients with hepatic impairment.

Drug-drug Interactions
In vitro studies using human liver microsomes indicate that fenofibric acid is not an inhibitor of cytochrome (CYP) P450 isoforms CYP3A4, CYP2D6, CYP2E1, or CYP1A2. It is a weak inhibitor of CYP2C8, CYP2C19, and CYP2A6, and mild-to-moderate inhibitor of CYP2C9 at therapeutic concentrations.

Comparison of atorvastatin exposures when atorvastatin (80 mg QD for 10 days) is given in combination with fenofibric acid (Trilipix 135 mg QD for 10 days) and ezetimibe (10 mg QD for 10 days) versus when atorvastatin is given in combination with ezetimibe only (ezetimibe 10 mg QD and atorvastatin, 80 mg QD for 10 days): The Cmax decreased by 1% for atorvastatin and ortho-hydroxy-atorvastatin and increased by 2% for parahydroxy-atorvastatin. The AUC decreased 6% and 9% for atorvastatin and orthohydroxy-atorvastatin, respectively, and did not change for para-hydroxy-atorvastatin.

Comparison of ezetimibe exposures when ezetimibe (10 mg QD for 10 days) is given in combination with fenofibric acid (Trilipix 135 mg QD for 10 days) and atorvastatin (80 mg QD for 10 days) versus when ezetimibe is given in combination with atorvastatin only (ezetimibe 10 mg QD and atorvastatin, 80 mg QD for 10 days): The Cmax increased by 26% and 7% for total and free ezetimibe, respectively. The AUC increased by 27% and 12% for total and free ezetimibe, respectively.

Table 3 describes the effects of co-administered drugs on fenofibric acid systemic exposure. Table 4 describes the effects of co-administered fenofibric acid on other drugs.

Table 3. Effects of Co-Administered Drugs on Fenofibric Acid Systemic Exposure from Trilipix or Fenofibrate Administration
Co-Administered Drug | Dosage Regimen of Co-Administered Drug | Dosage Regimen of Trilipix or Fenofibrate | Changes in Fenofibric Acid Exposure
 |  |  | AUC | Cmax
Lipid-lowering agents
Rosuvastatin | 40 mg QD for 10 days | Trilipix 135 mg QD for 10 days | ↓2% | ↓2%
Atorvastatin | 20 mg QD for 10 days | Fenofibrate 160 mg^1 QD for 10 days | ↓2% | ↓4%
Atorvastatin + ezetimibe | Atorvastatin, 80 mg QD and ezetimibe, 10 mg QD for 10 days | Trilipix 135 mg QD for 10 days | ↑5% | ↑5%
Pravastatin | 40 mg as a single dose | Fenofibrate 3 x 67 mg^2 as a single dose | ↓1% | ↓2%
Fluvastatin | 40 mg as a single dose | Fenofibrate 160 mg^1 as a single dose | ↓2% | ↓10%
Simvastatin | 80 mg QD for 7 days | Fenofibrate 160 mg^1 QD for 7 days | ↓5% | ↓11%
Anti-diabetic agents
Glimepiride | 1 mg as a single dose | Fenofibrate 145 mg^1 QD for 10 days | ↑1% | ↓1%
Metformin | 850 mg TID for 10 days | Fenofibrate 54 mg^1 TID for 10 days | ↓9% | ↓6%
Rosiglitazone | 8 mg QD for 5 days | Fenofibrate 145 mg^1 QD for 14 days | ↑10% | ↑3%
Gastrointestinal agents
Omeprazole | 40 mg QD for 5 days | Trilipix 135 mg as a single dose fasting | ↑6% | ↑17%
Omeprazole | 40 mg QD for 5 days | Trilipix 135 mg as a single dose with food | ↑4% | ↓2%
^1 TriCor (fenofibrate) oral tablet
^2 TriCor (fenofibrate) oral micronized capsule

Table 4. Effects of Trilipix or Fenofibrate Co-Administration on Systemic Exposure of Other Drugs
Dosage Regimen of Trilipix or Fenofibrate | Dosage Regimen of Co-Administered Drug | Change in Co-Administered Drug Exposure
 |  | Analyte | AUC | Cmax
Lipid-lowering agents
Trilipix 135 mg QD for 10 days | Rosuvastatin, 40 mg QD for 10 days | Rosuvastatin | ↑6% | ↑20%
Fenofibrate 160 mg^1 QD for 10 days | Atorvastatin, 20 mg QD for 10 days | Atorvastatin | ↓17% | 0%
Fenofibrate 3 x 67 mg^2 as a single dose | Pravastatin, 40 mg as a single dose | Pravastatin | ↑13% | ↑13%
 |  | 3α-Hydroxyl-iso-pravastatin | ↑26% | ↑29%
Fenofibrate 160 mg^1 as a single dose | Fluvastatin, 40 mg as a single dose | (+)-3R, 5S-Fluvastatin | ↑15% | ↑16%
Fenofibrate 160 mg^1 QD for 7 days | Simvastatin, 80 mg QD for 7 days | Simvastatin acid | ↓36% | ↓11%
 |  | Simvastatin | ↓11% | ↓17%
 |  | Active HMG-CoA Inhibitors | ↓12% | ↓1%
 |  | Total HMG-CoA Inhibitors | ↓8% | ↓10%
Anti-diabetic agents
Fenofibrate 145 mg^1 QD for 10 days | Glimepiride, 1 mg as a single dose | Glimepiride | ↑35% | ↑18%
Fenofibrate 54 mg^1 TID for 10 days | Metformin, 850 mg TID for 10 days | Metformin | ↑3% | ↑6%
Fenofibrate 145 mg^1 QD for 14 days | Rosiglitazone, 8 mg QD for 5 days | Rosiglitazone | ↑6% | ↓1%
^1 TriCor (fenofibrate) oral tablet
^2 TriCor (fenofibrate) oral micronized capsule

13 NONCLINICAL TOXICOLOGY

13.1 Carcinogenesis, Mutagenesis, Impairment of Fertility

Trilipix (fenofibric acid)

No carcinogenicity and fertility studies have been conducted with choline fenofibrate or fenofibric acid. However, because fenofibrate is rapidly converted to its active metabolite, fenofibric acid, either during or immediately following absorption both in animals and humans, studies conducted with fenofibrate are relevant for the assessment of the toxicity profile of fenofibric acid. A similar toxicity spectrum is expected after treatment with either Trilipix or fenofibrate.

Fenofibrate

Two dietary carcinogenicity studies have been conducted in rats with fenofibrate. In the first 24-month study, rats were dosed with fenofibrate at 10, 45, and 200 mg/kg/day, approximately 0.3, 1, and 6 times the maximum recommended human dose (MRHD), based on body surface area comparisons (mg/m^2). At a dose of 200 mg/kg/day (6 times the MRHD), the incidence of liver carcinomas was significantly increased in both sexes. A statistically significant increase in pancreatic carcinomas was observed in males at 1 and 6 times the MRHD; an increase in pancreatic adenomas and benign testicular interstitial cell tumors was observed at 6 times the MRHD in males.

A 117-week carcinogenicity study was conducted in rats comparing three drugs: fenofibrate 10 and 60 mg/kg/day (0.3 and 2 times the MRHD), clofibrate (400 mg/kg/day; 2 times the human dose), and gemfibrozil (250 mg/kg/day; 2 times the human dose, based on mg/m^2 surface area). Fenofibrate increased pancreatic acinar adenomas in both sexes and testicular interstitial cell tumors in males at 2 times the MRHD. Clofibrate increased hepatocellular carcinoma and pancreatic acinar adenomas in males and hepatic neoplastic nodules in females. Gemfibrozil increased hepatic neoplastic nodules in males and females, while all three drugs increased testicular interstitial cell tumors in males.

In an 80-week study in mice, fenofibrate 10, 45, and 200 mg/kg/day (approximately 0.2, 1, and 3 times the MRHD on the basis of mg/m^2 surface area) significantly increased the liver carcinomas in both sexes at 3 times the MRHD. In a second 93-week study at 10, 60, and 200 mg/kg/day, fenofibrate significantly increased the liver carcinomas in male and female mice at 3 times the MRHD.

Electron microscopy studies have demonstrated peroxisomal proliferation following fenofibrate administration to the rat. An adequate study to test for peroxisome proliferation in humans has not been done, but changes in peroxisome morphology and numbers have been observed in humans after treatment with other members of the fibrate class when liver biopsies were compared before and after treatment in the same individual.

Fenofibrate has been demonstrated to be devoid of mutagenic potential in the following tests: Ames, and micronucleus in vivo/rat. In addition, fenofibric acid, has been demonstrated to be devoid of mutagenic potential in the following tests: Ames, mouse lymphoma, chromosomal aberration and sister chromatid exchange in human lymphocytes, and unscheduled DNA synthesis in primary rat hepatocytes.

In a fertility study, rats were given oral dietary doses of fenofibrate. Males received doses for 61 days prior to mating and females for 15 days prior to mating through weaning, which resulted in no adverse effect on fertility at doses up to 300 mg/kg/day (~10 times the MRHD, based on mg/m^2 surface area comparisons).

14 CLINICAL STUDIES

14.1 Co-Administration Therapy with Statins

Efficacy and safety of Trilipix co-administered with statins were assessed in three 12-week, double-blind, controlled Phase 3 studies and one 52-week, long-term, open-label extension study in 2698 patients with mixed dyslipidemia. Patients were required to meet the following fasting lipid entry criteria: TG ≥ 150 mg/dL, and HDL-C < 40 mg/dL (males) and < 50 mg/dL (females), and LDL-C ≥ 130 mg/dL. The three multicenter, randomized, double-blind, controlled studies had similar designs, differing primarily in the statin used for combination therapy/monotherapy. Each study compared the effects of 135 mg Trilipix co-administered with either a low dose or a moderate dose of statin with Trilipix monotherapy and statin monotherapy at the corresponding dose on CHD lipid risk factors. A smaller group of patients received a high dose of statin monotherapy. In study 1, patients received Trilipix co-administered with 10 mg or 20 mg rosuvastatin. In study 2, patients received Trilipix co-administered with 20 mg or 40 mg simvastatin. In study 3, patients received Trilipix co-administered with 20 mg or 40 mg atorvastatin.

Patients were enrolled for a total of approximately 22 weeks, consisting of a 6-week diet run-in/washout period, a 12-week treatment period, and a 30-day safety follow up period. Patients who completed the 12-week treatment period were eligible to participate in the 52-week long-term extension study. Of the 2698 randomized and treated subjects in the controlled studies, 51.6% were female and 48.4% were male; 92.6% of all subjects were White, 4.7% were Black, and 2.8% were of other races. Hispanics comprised 9.9% of the study population. Mean age was 54.9 years.

The primary efficacy endpoints for all three studies were mean percent changes from baseline to final value in HDL-C, TG, and LDL-C. For each statin dose co-administered with Trilipix, there were three primary comparisons. For HDL-C and TG, Trilipix co-administered with each statin dose was compared with statin monotherapy at the corresponding dose. For LDL-C, Trilipix co-administered with each statin dose was compared with Trilipix monotherapy. In order to declare combination therapy successful for a particular statin dose, all three primary comparisons were required to demonstrate superiority of the combination therapy over the corresponding monotherapy. The primary efficacy results were consistent in the three studies and were confirmed by the pooled analysis of the three studies. The results from the individual studies and the pooled analysis demonstrated that Trilipix co-administered with low-dose statins and moderate-dose statins was superior to the corresponding monotherapy. Statistically significant differences were observed for all three primary efficacy comparisons for both doses of combination therapy in all three double-blind, controlled studies as well as the pooled analysis.

In the pooled analysis, Trilipix co-administered with both low-dose statins and moderate-dose statins resulted in mean percent increases (18.1% and 17.5%) in HDL-C and mean percent decreases (-43.9% and -42.0%) in TG that were significantly greater than the corresponding dose of statin monotherapy (7.4% and 8.7% for HDL-C; -16.8% and -23.7% for TG). In addition, both doses of combination therapy resulted in mean percent decreases (-33.1% and -34.6%) in LDL-C that were significantly greater than Trilipix monotherapy (-5.1%). The results of the pooled analysis are described in Table 5.

Table 5.Mean Percent Change from Baseline to the Final Value in HDL-C, TG, and LDL-C (Pooled Double-Blind, Controlled Studies)
 | Trilipix | Low-Dose Statin | Trilipix + Low-Dose Statin | Between-group ∆ (p-value) | Moderate-Dose Statin | Trilipix + Moderate-Dose Statin | Between-group ∆ (p-value) | High-Dose Statin
HDL-C (mg/dL) | (N = 420) | (N = 455) | (N = 423) |  | (N = 430) | (N = 422) |  | (N = 217)
BL mean | 38.4 | 38.4 | 38.2 |  | 38.4 | 38.1 |  | 38.0
Mean % ∆ | 16.3% | 7.4% | 18.1% | 10.7%a (< 0.001) | 8.7% | 17.5% | 8.8%a (< 0.001) | 7.9%
TG (mg/dL) | (N = 459) | (N = 477) | (N = 470) |  | (N = 472) | (N = 462) |  | (N = 235)
BL mean | 280.7 | 286.1 | 282.1 |  | 287.9 | 286.1 |  | 282.5
Mean % ∆ | -31.0% | -16.8% | -43.9% | -27.2%a (< 0.001) | -23.7% | -42.0% | -18.3%a (< 0.001) | -28.1%
LDL-C (mg/dL) | (N = 427) | (N = 463) | (N = 436) |  | (N = 439) | (N = 434) |  | (N = 225)
BL mean | 158.4 | 153.8 | 155.7 |  | 158.0 | 156.4 |  | 156.1
Mean % ∆ | -5.1% | -33.9% | -33.1% | -28.0%b (< 0.001) | -40.6% | -34.6% | -29.5%b (< 0.001) | -47.1%
a Combination therapy vs. corresponding statin monotherapy
b Combination therapy vs. Trilipix monotherapy
Low-dose statin = rosuvastatin 10 mg, simvastatin 20 mg, or atorvastatin 20 mg
Moderate-dose statin = rosuvastatin 20 mg, simvastatin 40 mg, or atorvastatin 40 mg
High-dose statin = rosuvastatin 40 mg, simvastatin 80 mg, or atorvastatin 80 mg
BL = Baseline
% ∆ = Percent change from baseline to final value

Secondary efficacy endpoints in all three double-blind, controlled studies were percent changes in non-HDL-C (Trilipix co-administered with statin compared to Trilipix monotherapy and corresponding statin monotherapy), and percent changes in VLDL-C, Total-C, and Apo B (Trilipix co-administered with statin compared to corresponding statin monotherapy). Co-administration of Trilipix with statins resulted in the following changes in secondary parameters (Table 6).

Table 6. Percent Change from Baseline to the Final Value in Non-HDL-C, VLDL-C, Total-C, and Apo B (Pooled Double-Blind, Controlled Studies)
Secondary Endpoints | Trilipix | Low-Dose Statin | Trilipix + Low-Dose Statin | Between-group ∆ | Moderate-Dose Statin | Trilipix + Moderate-Dose Statin | Between-group ∆ | High-Dose Statin
Non HDL-C (mg/dL) | (N = 420) | (N = 454) | (N = 422) |  | (N = 431) | (N = 420) |  | (N = 217)
BL mean | 222.5 | 217.6 | 219.9 |  | 222.4 | 218.9 |  | 220.2
Mean % ∆ | -17.3% | -34.9% | -40.4% | -23.1%a -5.5%b | -42.4% | -42.0% | -24.8%a 0.4%b | -47.3%
VLDL-C (mg/dL) | (N = 449) | (N = 463) | (N = 455) |  | (N = 458) | (N = 449) |  | (N = 232)
BL mean | 65.0 | 66.0 | 65.5 |  | 67.8 | 64.5 |  | 66.1
Mean % ∆ | -34.2% | -32.1% | -50.0% | -18.0%b | -38.9% | -51.2% | -12.3%b | -42.1%
Total-C (mg/dL) | (N = 459) | (N = 477) | (N = 469) |  | (N = 472) | (N = 462) |  | (N = 235)
BL mean | 260.9 | 257.0 | 258.6 |  | 261.3 | 257.3 |  | 258.8
Mean % ∆ | -12.4% | -28.7% | -31.5% | -2.8%b | -34.7% | -33.3% | 1.4%b | -39.5%
Apo B (mg/dL) | (N = 455) | (N = 470) | (N = 465) |  | (N = 468) | (N = 455) |  | (N = 229)
BL mean | 146.2 | 145.0 | 146.1 |  | 147.1 | 145.0 |  | 146.0
Mean % ∆ | -15.6% | -31.1% | -36.3% | -5.2%b | -36.9% | -36.7% | 0.2%b | -42.4%
a Trilipix + statin vs. Trilipix monotherapy
b Trilipix + statin vs. corresponding statin monotherapy
Low-dose statin = rosuvastatin 10 mg, simvastatin 20 mg, or atorvastatin 20 mg
Moderate-dose statin = rosuvastatin 20 mg, simvastatin 40 mg, or atorvastatin 40 mg
High-dose statin = rosuvastatin 40 mg, simvastatin 80 mg, or atorvastatin 80 mg
BL = Baseline
% ∆ = Percent change from baseline to final value

A total of 1895 patients who completed 12 weeks of treatment in the double-blind, controlled studies were treated in the 52-week, long-term extension study. Patients received Trilipix co-administered with the moderate-dose of the statin that had been used in the double-blind, controlled study in which they were enrolled. Whether combination therapy was initiated during the double-blind, controlled studies or introduced during the long-term extension study, the treatment effect of combination therapy was observed within four weeks, and was sustained over the duration of treatment in the long-term study. A total of 568 patients completed 52 weeks of treatment with Trilipix co-administered with statins. Mean 52-week values and mean percent change from baseline (at time of enrollment in randomized controlled trials) were 91.7 mg/dL (-38.2%) for LDL-C, 47.3 mg/dL (+24.0%) for HDL-C, 135.5 mg/dL (-47.6%) for TG, 117.9 mg/dL (-45.7%) for non-HDL-C, 26.2 mg/dL (-53.1%) for VLDL-C, 165.2 mg/dL (-35.4%) for Total-C, and 81.4 mg/dL (-43.6%) for Apo B.

14.2 Hypertriglyceridemia

The effects of fenofibrate on serum triglycerides were studied in two randomized, double-blind, placebo-controlled clinical trials of 147 hypertriglyceridemic patients. Patients were treated for eight weeks under protocols that differed only in that one entered patients with baseline TG levels of 500 to 1500 mg/dL, and the other TG levels of 350 to 500 mg/dL. In patients with hypertriglyceridemia and normal cholesterolemia with or without hyperchylomicronemia, treatment with fenofibrate at dosages equivalent to 135 mg once daily of Trilipix decreased primarily VLDL-TG and VLDL-C. Treatment of patients with elevated TG often results in an increase of LDL-C (Table 7).

Table 7. Effects of Fenofibrate in Patients With Hypertriglyceridemia
Study 1 | Placebo |  |  |  | Fenofibrate
Baseline TG levels 350 to 499 mg/dL | N | Baseline Mean (mg/dL) | Endpoint Mean (mg/dL) | Mean % Change | N | Baseline Mean (mg/dL) | Endpoint Mean (mg/dL) | Mean % Change
Triglycerides | 28 | 449 | 450 | -0.5 | 27 | 432 | 223 | -46.2*
VLDL Triglycerides | 19 | 367 | 350 | 2.7 | 19 | 350 | 178 | -44.1*
Total Cholesterol | 28 | 255 | 261 | 2.8 | 27 | 252 | 227 | -9.1*
HDL Cholesterol | 28 | 35 | 36 | 4 | 27 | 34 | 40 | 19.6*
LDL Cholesterol | 28 | 120 | 129 | 12 | 27 | 128 | 137 | 14.5
VLDL Cholesterol | 27 | 99 | 99 | 5.8 | 27 | 92 | 46 | -44.7*
Study 2 | Placebo |  |  |  | Fenofibrate
Baseline TG levels 500 to 1500 mg/dL | N | Baseline Mean (mg/dL) | Endpoint Mean (mg/dL) | Mean % Change | N | Baseline Mean (mg/dL) | Endpoint Mean (mg/dL) | Mean % Change
Triglycerides | 44 | 710 | 750 | 7.2 | 48 | 726 | 308 | -54.5*
VLDL Triglycerides | 29 | 537 | 571 | 18.7 | 33 | 543 | 205 | -50.6*
Total Cholesterol | 44 | 272 | 271 | 0.4 | 48 | 261 | 223 | -13.8*
HDL Cholesterol | 44 | 27 | 28 | 5.0 | 48 | 30 | 36 | 22.9*
LDL Cholesterol | 42 | 100 | 90 | -4.2 | 45 | 103 | 131 | 45.0*
VLDL Cholesterol | 42 | 137 | 142 | 11.0 | 45 | 126 | 54 | -49.4*
* = p < 0.05 vs. Placebo

14.3 Primary Hypercholesterolemia (Heterozygous Familial and Nonfamilial) and Mixed Dyslipidemia

The effects of fenofibrate at a dose equivalent to Trilipix 135 mg once daily were assessed from four randomized, placebo-controlled, double-blind, parallel-group studies including patients with the following mean baseline lipid values: Total-C 306.9 mg/dL; LDL-C 213.8 mg/dL; HDL-C 52.3 mg/dL; and triglycerides 191.0 mg/dL. Fenofibrate therapy lowered LDL-C, Total-C, and the LDL-C/HDL-C ratio. Fenofibrate therapy also lowered triglycerides and raised HDL-C (Table 8).

Table 8. Mean Percent Change in Lipid Parameters at End of Treatment†
Treatment Group | Total-C (mg/dL) | LDL-C (mg/dL) | HDL-C (mg/dL) | TG (mg/dL)
Pooled Cohort
Mean baseline lipid values (n = 646) | 306.9 | 213.8 | 52.3 | 191.0
All Fenofibrate (n = 361) | -18.7%* | -20.6%* | +11.0%* | -28.9%*
Placebo (n = 285) | -0.4% | -2.2% | +0.7% | +7.7%
Baseline LDL-C > 160 mg/dL and TG < 150 mg/dL
Mean baseline lipid values (n = 334) | 307.7 | 227.7 | 58.1 | 101.7
All Fenofibrate (n = 193) | -22.4%* | -31.4%* | +9.8%* | -23.5%*
Placebo (n = 141) | +0.2% | -2.2% | +2.6% | +11.7%
Baseline LDL-C > 160 mg/dL and TG ≥ 150 mg/dL
Mean baseline lipid values (n = 242) | 312.8 | 219.8 | 46.7 | 231.9
All Fenofibrate (n = 126) | -16.8%* | -20.1%* | +14.6%* | -35.9%*
Placebo (n = 116) | -3.0% | -6.6% | +2.3% | +0.9%
† Duration of study treatment was 3 to 6 months
* p = < 0.05 vs. Placebo

In a subset of the subjects, measurements of Apo B were conducted. Fenofibrate treatment significantly reduced Apo B from baseline to endpoint as compared with placebo (-25.1% vs. 2.4%, p < 0.0001, n = 213 and 143, respectively).

16 HOW SUPPLIED/STORAGE AND HANDLING

Trilipix (fenofibric acid) delayed release capsules are supplied as followed:

- Trilipix 135 mg fenofibric acid delayed release capsules have a blue cap imprinted in white ink the Abbott “A” logo and a yellow body imprinted in black ink the number “135”. Each hard gelatin capsule contains enteric coated white to off white bi-convex round mini-tablets. The delayed release capsules are available in bottles of 30 (NDC 54868-5986-0) and in bottles of 90 (NDC54868-5986-1).

Storage and Handling

Store Trilipix 135 mg delayed release capsules at 25°C (77°F); excursions permitted to 15°-30°C (59° to 86°F) [See USP controlled room temperature]. Keep out of the reach of children. Protect from moisture.

17 PATIENT COUNSELING INFORMATION

See Medication Guide

17.1 Patient Counseling

Patients should be advised:

- of the potential benefits and risks of Trilipix.
- to read the Medication Guide before starting Trilipix therapy and to reread it each time the prescription is renewed.
- of medications that should not be taken in combination with Trilipix.
- to continue to follow an appropriate lipid-modifying diet while taking Trilipix.
- to take Trilipix once daily, without regard to food, at the prescribed dose, swallowing each capsule whole. If Trilipix is co-administered with a statin, they may be taken together.
- to return for routine monitoring.
- to inform their physician of all medications, supplements, and herbal preparations they are taking and any change to their medical condition. Patients should also be advised to inform their physicians prescribing a new medication that they are taking Trilipix.
- to inform their physician of any muscle pain, tenderness, or weakness; onset of abdominal pain; or any other new symptoms.

Manufactured for Abbott Laboratories, North Chicago, IL 60064, U.S.A.

by Fournier Laboratories Ireland Limited, Anngrove, Carrigtwohill Co. Cork, Ireland,

or Abbott Pharmaceutical PR Ltd., Barceloneta, PR 00617.

Relabeling and Repackaging by:
Physicians Total Care, Inc.
Tulsa, Oklahoma 74146

MEDICATION GUIDE

Trilipix

(try-lip-iks)

(fenofibric acid, delayed release capsules)

Read this Medication Guide before you start taking Trilipix and each time you get a refill. There may be new information. This information does not take the place of talking to your healthcare provider about your medical condition or your treatment.

What is the most important information I should know about Trilipix?

Trilipix can be used with other cholesterol-lowering medicines called statins. Statins include:

- atorvastatin (Lipitor, Caduet)
- fluvastatin (Lescol, Lescol XL)
- lovastatin (Altoprev, Mevacor, Advicor)
- pitavastatin (Livalo)
- pravastatin (Pravachol)
- rosuvastatin (Crestor)
- simvastatin (Zocor, Simcor, Vytorin)

Statins can cause muscle pain, tenderness or weakness, which may be symptoms of a rare but serious muscle condition called rhabdomyolysis. In some cases rhabdomyolysis can cause kidney damage and death. The risk of rhabdomyolysis may be higher when Trilipix is given with statins. If you take a statin, tell your healthcare provider.

Other medicines or large amounts of grapefruit juice (more than a quart) may raise the levels of statins in your body, and could then raise the risk of muscle problems. Tell your healthcare provider if you are taking any medicines listed below.

- Heart medicine
- Stomach medicine
- Antibiotic
- Anti-fungal
- Cholesterol-lowering medicine
- Hormones
- HIV/AIDS medicine
- Antidepressant
- Immunosuppressant
- Anti-seizure medicine

Ask your healthcare provider or pharmacist for a list of these medicines, if you are not sure.

Tell your healthcare provider if you drink grapefruit juice.

What is Trilipix?

Trilipix is a prescription medicine used to treat cholesterol in the blood by lowering the total amount of triglycerides and LDL (bad) cholesterol, and increasing the HDL (good) cholesterol. Trilipix has not been shown to lower your risk of having heart problems or a stroke. You should be on a low fat and low cholesterol diet while you take Trilipix.

The safety and effectiveness of Trilipix in children is not known.

Who should not take Trilipix?

Do not take Trilipix if you:

- are allergic to fenofibric acid, or any of the ingredients in Trilipix. See the end of this Medication Guide for a list of all the ingredients in Trilipix.
- have severe kidney disease.
- have liver disease.
- have gallbladder disease.
- are a nursing mother.

Talk to your healthcare provider before you take Trilipix if you have any of these conditions.

What should I tell my healthcare provider before taking Trilipix?

Before taking Trilipix, tell your healthcare provider about all your medical conditions, including if you:

- are allergic to any medicines.
- have ever had kidney problems.
- have ever had liver problems.
- have ever had gallbladder problems.
- are pregnant or if you plan to become pregnant. It is not known if Trilipix will harm your unborn baby.
- are breastfeeding or plan to breastfeed. It is not known if Trilipix passes into your breast milk. You and your healthcare provider should decide if you will take Trilipix or breastfeed. You should not do both.

Tell your healthcare provider about all the medicines you take, including prescription and non-prescription medicines, vitamins and herbal supplements.

Using Trilipix with certain other medicines can affect the way these medicines work and other medicines may affect how Trilipix works. In some cases, using Trilipix with other medicines can cause serious side effects.

Know all the medicines you take. Keep a list of them and show it to your healthcare provider when you get a new medicine.

It is especially important to tell your healthcare provider if you take any of the medicines mentioned in, "What is the most important information I should know about Trilipix?" or any of the medicines listed below:

- anticoagulants, also known as blood thinners (warfarin, Coumadin)
- bile acid resins
- cyclosporine

Ask your healthcare provider if you are not sure if your medicine is one of these.

How should I take Trilipix?

- You should be on a low fat and low cholesterol diet while you take Trilipix.
- Take Trilipix one time each day as prescribed by your healthcare provider.
- Take Trilipix with or without food.
- Swallow Trilipix capsules whole. Do not break, crush, dissolve, or chew Trilipix capsules before swallowing. If you cannot swallow Trilipix capsules whole, tell your healthcare provider, you may need a different medicine.
- If you take a medicine called a statin, you can take Trilipix and your statin at the same time of day.
- If you miss a dose of Trilipix, take it as soon as you remember. If it is almost time for your next dose, just skip the missed dose. Take the next dose at your regular time. If you are not sure about your dosing, call your healthcare provider. Do not take more than one dose of Trilipix a day unless your healthcare provider tells you to.
- If you take too much Trilipix, contact your healthcare provider or your local emergency department.
- Do not change your dose or stop Trilipix unless your healthcare provider tells you to.
- Your healthcare provider may do blood tests before you start taking Trilipix and during treatment. See your healthcare provider regularly to check your cholesterol and triglyceride levels and to check for side effects.

What are the possible side effects with Trilipix?

Trilipix may cause serious side effects, including:

- muscle pain, tenderness, or weakness. See "What is the most important information that I should know about Trilipix?"
- tiredness and fever.
- abdominal pain, nausea, or vomiting. These may be signs of inflammation (swelling) of the gallbladder or pancreas.

Call your healthcare provider right away if you have any of these serious side effects.

The most common side effects with Trilipix include:

- headache
- heartburn (indigestion)
- nausea
- muscle aches
- increases in muscle or liver enzymes that are measured by blood tests

Tell your healthcare provider if you have any side effect that bothers you or that does not go away. These are not all the possible side effects of Trilipix. For more information, ask your healthcare provider or pharmacist.

Call your doctor for medical advice about side effects. You may report side effects to FDA at 1-800-FDA-1088.

How do I store Trilipix?

- Store Trilipix between 59° to 86° F (15° to 30° C).
- Protect Trilipix from moisture.

Keep Trilipix and all medicines out of the reach of children.

General information about the safe and effective use of Trilipix

Medicines are sometimes prescribed for conditions that are not mentioned in the Medication Guide. Do not use Trilipix for a condition for which it was not prescribed. Do not give Trilipix to other people, even if they have the same condition you have. It may harm them.

This Medication Guide summarizes the most important information about Trilipix. If you would like more information, talk to your healthcare provider. You can also ask your pharmacist or healthcare provider for information that is written for health professionals.

For more information go to www.Trilipix.com or call 1-800-633-9110.

What are the ingredients in Trilipix?

Active Ingredient: Fenofibric acid

Inactive Ingredients: Hypromellose, povidone, water, hydroxylpropyl cellulose, colloidal silicon dioxide, sodium stearyl fumarate, methacrylic acid copolymer, talc, triethyl citrate, gelatin, titanium dioxide, and yellow iron oxide. Additionally, the 45 mg capsule shell contains black iron oxide and red iron oxide, and the 135 mg capsule shell contains FD&C Blue #2.

©Abbott

Manufactured for Abbott Laboratories, North Chicago, IL 60064, U.S.A. by Fournier Laboratories Ireland Limited, Anngrove, Carrigtwohill Co. Cork, Ireland, or Abbott Pharmaceutical PR Ltd., Barceloneta, PR 00617.

Rev. 09/2011 Abbott Laboratories

This Medication Guide has been approved by the U.S. Food and Drug Administration.

PACKAGE LABEL

Trilipix®

Fenofibric Acid Delayed Release Capsules 135 mg*

Dispense Medication Guide (see package insert) with product

Rx only